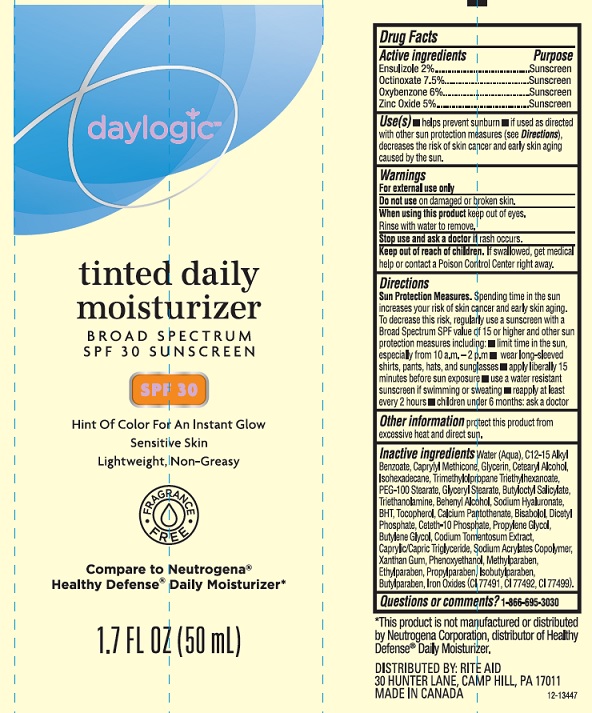 DRUG LABEL: Daylogic Tinted Daily Moisturizer SPF 30
NDC: 11822-3430 | Form: LOTION
Manufacturer: Rite Aid Corporation
Category: otc | Type: HUMAN OTC DRUG LABEL
Date: 20170814

ACTIVE INGREDIENTS: ENSULIZOLE 20 mg/1 mL; OCTINOXATE 75 mg/1 mL; OXYBENZONE 60 mg/1 mL; ZINC OXIDE 50 1/1 mL
INACTIVE INGREDIENTS: WATER; ALKYL (C12-15) BENZOATE; CAPRYLYL TRISILOXANE; GLYCERIN; CETOSTEARYL ALCOHOL; ISOHEXADECANE; TRIMETHYLOLPROPANE TRIETHYLHEXANOATE; PEG-100 STEARATE; GLYCERYL MONOSTEARATE; BUTYLOCTYL SALICYLATE; TROLAMINE; DOCOSANOL; HYALURONATE SODIUM; BUTYLATED HYDROXYTOLUENE; .ALPHA.-TOCOPHEROL; CALCIUM PANTOTHENATE; LEVOMENOL; DIHEXADECYL PHOSPHATE; CETETH-10 PHOSPHATE; PROPYLENE GLYCOL; BUTYLENE GLYCOL; CODIUM TOMENTOSUM; MEDIUM-CHAIN TRIGLYCERIDES; SODIUM ACRYLATE; XANTHAN GUM; PHENOXYETHANOL; METHYLPARABEN; ETHYLPARABEN; PROPYLPARABEN; ISOBUTYLPARABEN; BUTYLPARABEN; FERRIC OXIDE RED; FERRIC OXIDE YELLOW; FERROSOFERRIC OXIDE

Drug Facts

Active ingredients

Ensulizole 2%

Octinoxate 7.5%

Oxybenzone 6%

Zinc Oxide 5%

Purpose

Sunscreen

Uses

- helps prevent sunburn
- if used as directed with other sun protectio measures (see Directions), decreases the risk of skin cancer and early skin aging caused by the sun.

Warnings

For external use only.

Do not use

on damaged or broken skin.

When using this product

keep out of eyes. Rinse with water to remove.

Sto use and ask a doctor if

rash occurs.

Keep out of reach of children.

If swallowed, get medical help or contact a Poison Control Center right away.

Directions

Sun Protection Measures. Spending time in the sun increases your risk of skin cancer and early skin aging. To decrease this risk, regularly use a sunscreen with a Broad Spectrum SPF value of 15 or higher and other sun protection measures including:

- limit time in sun, especially from 10 a.m. - 2 p.m.
- wear long-sleeved shirts, pants, hats, and sunglasses
- apply liberally 15 minutes before sun exposure
- use a water resistant sunscreen if swimming or sweating
- reapply at least every 2 hours
- children under 6 months: ask a doctor

Other information

protect this product from excessive heat and direct sun.

Inactive ingredients

Water (Aqua), C12-15 Alkyl Benzoate, Caprylyl Methicone, Glcerin, Cetearyl Alcohol, Isohexadecane, Trimethylolpropane Triethylhexanoate, PEG-100 Stearate, Glyceryl Stearate, Butyloctyl Salicylate, Triethanolamine, Calcium Pantothenate, Bisabolol, Dicetyl Phosphate, Ceteth-10 Phosphate, Propylene Glycol, Butylene Glycol, Codium Tomentosum Extract, Caprylic/Capric Triglyceride, Sodium Acrylates Copolymer, Xanthan Gum, Phenoxyethanol, Methylparaben, Ethylparaben, Propylparaben, Isobtuylparaben, Butylparaben, Iron Oxides (CI 77491, CI 77492, CI 77499).

Questions or comments?

1-866-695-3030